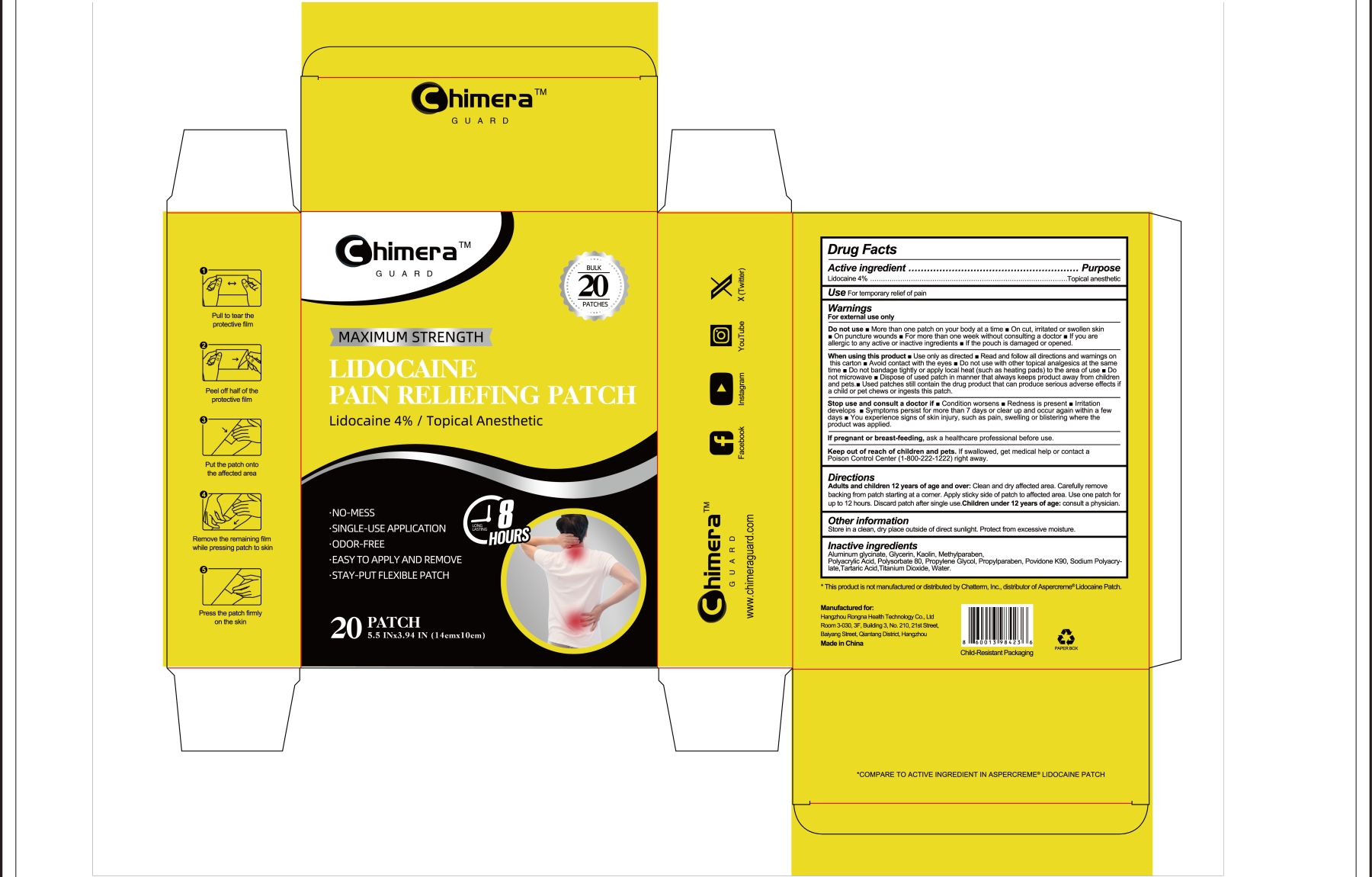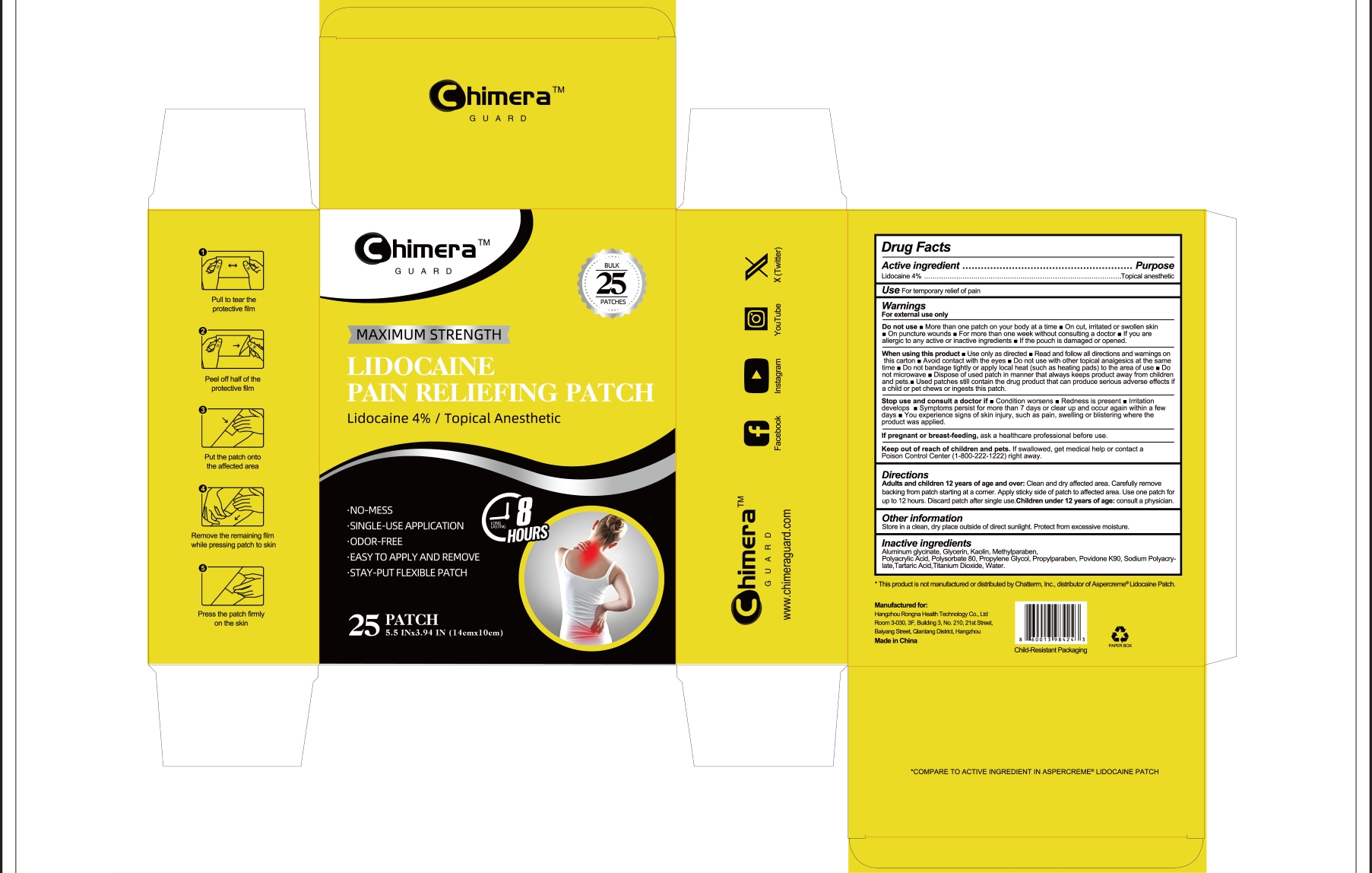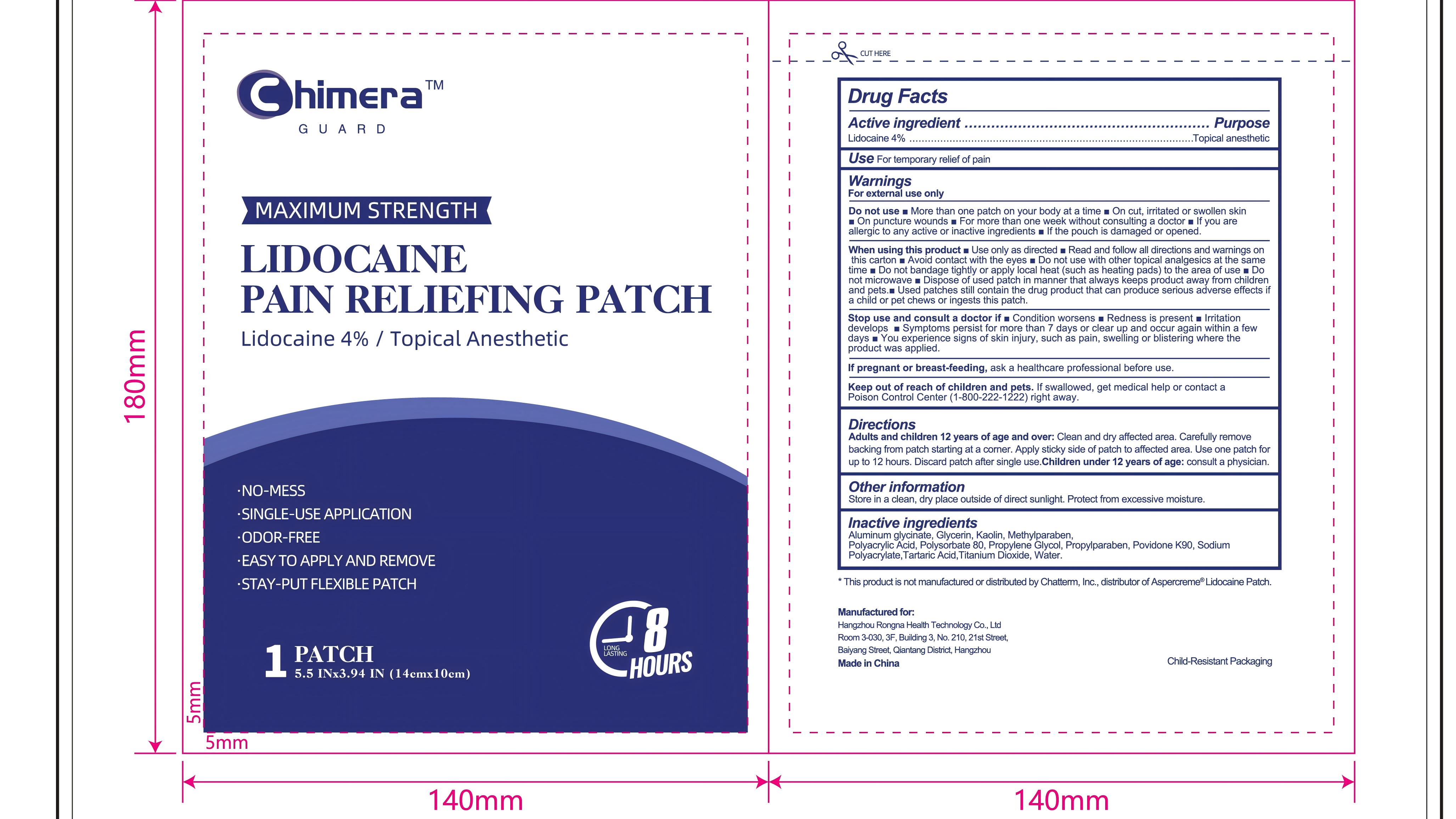 DRUG LABEL: Chimera GUARD
NDC: 85761-159 | Form: PATCH
Manufacturer: Hangzhou Rongna Health Technology Co., Ltd.
Category: otc | Type: HUMAN OTC DRUG LABEL
Date: 20250729

ACTIVE INGREDIENTS: LIDOCAINE 0.04 g/1 g
INACTIVE INGREDIENTS: GLYCERIN; POVIDONE K90; METHYLPARABEN; POLYSORBATE 80; PROPYLPARABEN; KAOLIN; TARTARIC ACID; WATER; PROPYLENE GLYCOL; POLYACRYLIC ACID (250000 MW); SODIUM POLYACRYLATE (2500000 MW); TITANIUM DIOXIDE; DIHYDROXYALUMINUM AMINOACETATE ANHYDROUS

Hangzhou Rongna Health Technology Co., Ltd
, LIDOCAINE PAIN RELIEFING PATCH
, Lidocaine 4%,20-25 Patches

Active Ingredient

Lidocaine 4% ...... Purpose: Topical Anesthetic

Purpose

Topical Anesthetic

Uses

For temporary relief of pain

Warnings

For external use only

Do not use

- More than 1 patch on your body at a time
- On cut,irritated orswollen skin
- On puncture wounds
- For more than oneweek without consulting a doctor
- if you are allergic to any active or inactive ingredients
- If the pouch is damaged or opened.

When using this product

- Use only as directed
- Read and follow all directions and warnings on this carton
- Avoid contact with the eyes
- Do not use with other topical analgesics at the same time
- Do not bandage tightly or apply local heat(such as heating pads) to the area of use
- Do not microwave
- Dispose of used patch in manner that always keeps product away from children and pets.
- Used patches still contain the drug product that can produce serious adverse effects if a child or pet chews or ingests this patch.

Stop use ... if

- Condition worsens
- Redness is present
- Irritationn develops
- Symptoms persist for more than 7 days or clear up and occur again within a few days
- You experience signs of skin injury,suchaspain,swelling or blistering where the
  product was applied

... ask a doctor if

Condition worsens
Redness is present
Irritationn develops
Symptoms persist for more than 7 days or clear up and occur again within a few days
You experience signs of skin injury,suchaspain,swelling or blistering where the product was applied

If pregnant or breast-feeding

ask a healthcare professional before use

Keep out of reach of children

If swallowed, get medical help or contact a Poison Control Center(1-800-222-1222) right away.

Directions

Adult and Children 12 years of age and over:

- Clean and dry affected area
- Carefully remove backing from patch starting at a corner
- Apply sticky side of patch to affected area.
- Use one patch forup to 12 hours
- Discard patch after single use

Children under 12 years of age: Consult a physician

Other information

Store ina clean,dry place outside of direct sunlight .Protect from excessive moisture.

Inactive Ingredients

Aluminum glycinate, Glycerin, Kaolin, Methylparaben, Polyacrylic Acid,Polysorbate 80, Propylene Glycol, , Propylparaben, Povidone K90, Sodium Polyacrylate, Tartaric Acid, Titanium Dioxide, Water

Questions or Comments

www.chimeraguard.com